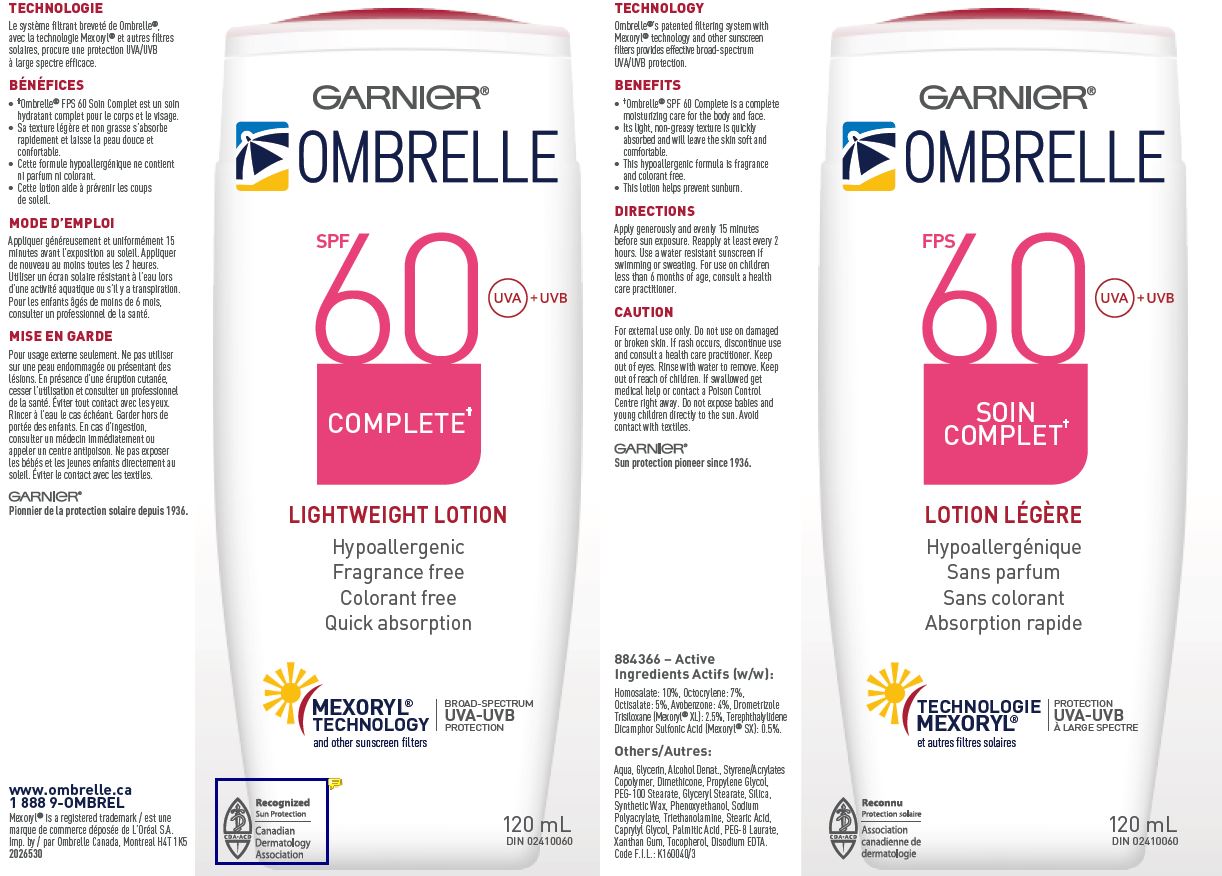 DRUG LABEL: Garnier Ombrelle SPF 60 Complete Lightweight
NDC: 49967-081 | Form: LOTION
Manufacturer: L'Oreal USA Products Inc
Category: otc | Type: HUMAN OTC DRUG LABEL
Date: 20260107

ACTIVE INGREDIENTS: HOMOSALATE 100 mg/1 mL; OCTOCRYLENE 70 mg/1 mL; octisalate 50 mg/1 mL; AVOBENZONE 40 mg/1 mL; DROMETRIZOLE TRISILOXANE 25 mg/1 mL; ECAMSULE 5 mg/1 mL
INACTIVE INGREDIENTS: WATER; GLYCERIN; ALCOHOL; STYRENE/ACRYLAMIDE COPOLYMER (500000 MW); DIMETHICONE; PROPYLENE GLYCOL; PEG-100 STEARATE; GLYCERYL MONOSTEARATE; SILICON DIOXIDE; PHENOXYETHANOL; TROLAMINE; STEARIC ACID; CAPRYLYL GLYCOL; PALMITIC ACID; PEG-8 LAURATE; XANTHAN GUM; TOCOPHEROL; EDETATE DISODIUM

Drug Facts

Active ingredients

Homosalate 10%

Octocrylene 7%

Octisalate 5%

Avobenzone 4%

Drometrizole Trisiloxane 2.5%

Terephthalylidene Dicamphor Sulfonic Acid 0.5%

Caution

For external use only. Do not use on damaged or broken skin. If rash occurs, discontinue use and consult a health care practitioner. Keep out of eyes. Rinse with water to remove. Keep out of reach of children. If swallowed get medical help or contact a Poison Control Centre right away. Do not expose babies and young children directly to the sun. Avoid contact with textiles.

Directions

Apply generously and evenly 15 minutes before sun exposure. Reapply at least every 2 hours. Use a water resistant sunscreen if swimming or sweating. For use on children less than 6 months of age, consult a health care practitioner.

Others

Aqua, Glycerin, Alcohol Denat., Styrene/Acrylates Copolymer, Dimethicone, Propylene Glycol, PEG-100 Stearate, Glyceryl Stearate, Silica, Synthetic Wax, Phenoxyethanol, Sodium Polyacrylate, Triethanolamine, Stearic Acid, Caprylyl Glycol, Palmitic Acid, PEG-8 Laurate, Xanthan Gum, Tocopherol, Disodium EDTA